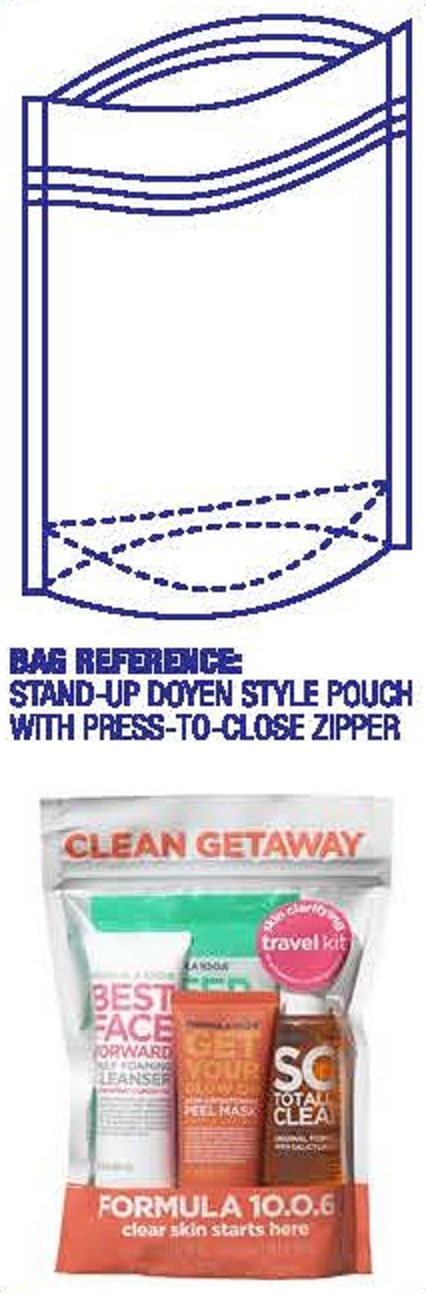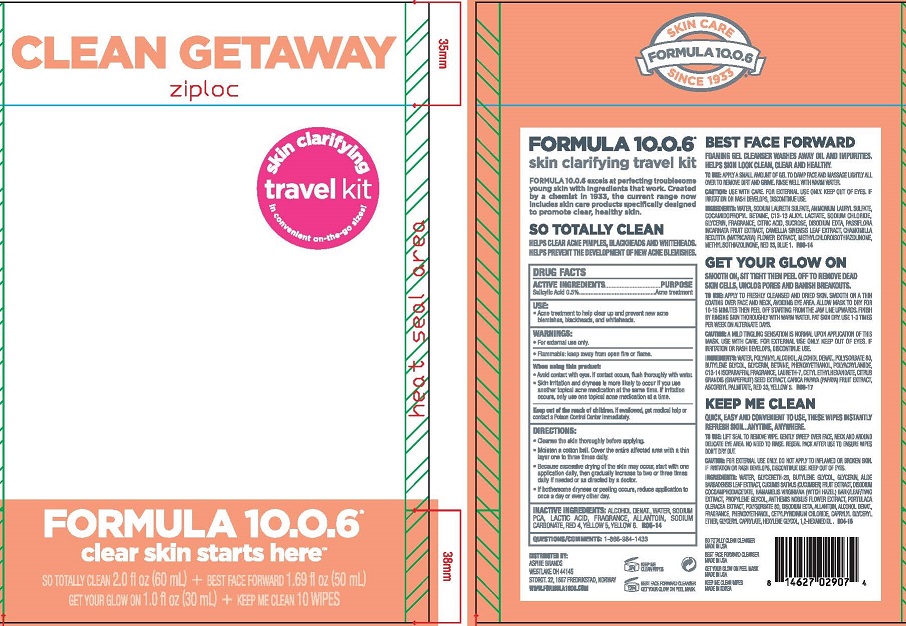 DRUG LABEL: CLEAN GETAWAY BAG
NDC: 70626-504 | Form: KIT | Route: TOPICAL
Manufacturer: ASPIRE BRANDS INC
Category: otc | Type: HUMAN OTC DRUG LABEL
Date: 20241206

ACTIVE INGREDIENTS: SALICYLIC ACID 0.5 g/100 mL
INACTIVE INGREDIENTS: ALCOHOL; WATER; SODIUM PYRROLIDONE CARBOXYLATE; LACTIC ACID; ALLANTOIN; SODIUM CARBONATE; FD&C RED NO. 4; FD&C YELLOW NO. 5; FD&C YELLOW NO. 6

ASPIRE BRANDS - CLEAN GETAWAY BAG (70626-504)

ACTIVE INGREDIENT

SALICYLIC ACID 0.5%

PURPOSE

ACNE TREATMENT

USE

ACNE TREATMENT TO HELP CLEAR UP AND PREVENT NEW ACNE BLEMISHES, BLACKHEADS, AND WHITEHEADS.

WARNINGS

- FOR EXTERNAL USE ONLY
- FLAMMABLE: KEEP AWAY FROM OPEN FIRE OR FLAME.

WHEN USING THIS PRODUCT

AVOID CONTACT WITH EYES. IF CONTACT OCCURS, FLUSH THOROUGHLU WITH WATER.
SKIN IRRITATION AND DRYNESS IS MORE LIKELY TO OCCUR IF YOU USE ANOTHER TOPICAL ACNE MEDICATION AT THE SAME TIME. IF IRRITATION OCCURS, ONLY USE ONE TOPICAL ACNE MEDICATION AT A TIME.

KEEP OUT OF REACH OF CHILDREN. IF SWALLOWED, GET MEDICAL HELP OR CONTACT A POISON CONTROL CENTER RIGHT AWAY.

DIRECTIONS

CLEAN THE SKIN THOROUGHLY BEFORE APPLYING THIS PRODUCT.
MOISTEN A COTTON BALL. COVER THE ENTIRE AFFECTED AREA WITH A THIN LAYER ONE TO THREE TIMES DAILY.
BECAUSE EXCESSIVE DRYING OF THE SKIN MAY OCCUR, START WITH ONE APPLICATION DAILY, THEN GRADUALLY INCREASE TO TWO OR THREE TIMES DAILY IF NEEDED OR AS DIRECTED BY A DOCTOR.
IF BOTHERSOME DRYNESS OR PEELING OCCURS, REDUCE APPLICATION TO ONCE A DAY OR EVERY OTHER DAY.

INACTIVE INGREDIENTS

ALCOHOL DENAT., WATER, SODIUM PCA, LACTIC ACID, FRAGRANCE, ALLANTOIN, SODIUM CARBONATE, RED 4, YELLOW 5, YELLOW 6.